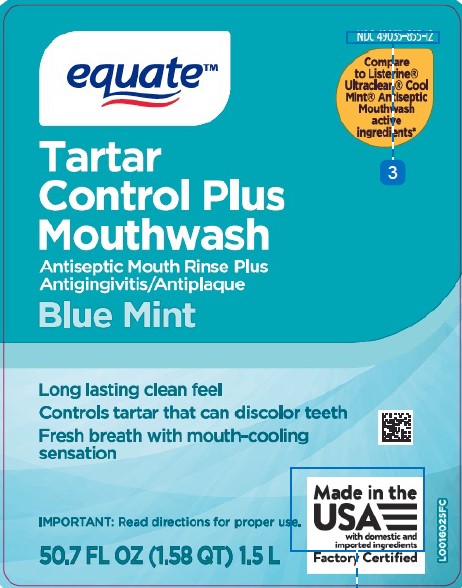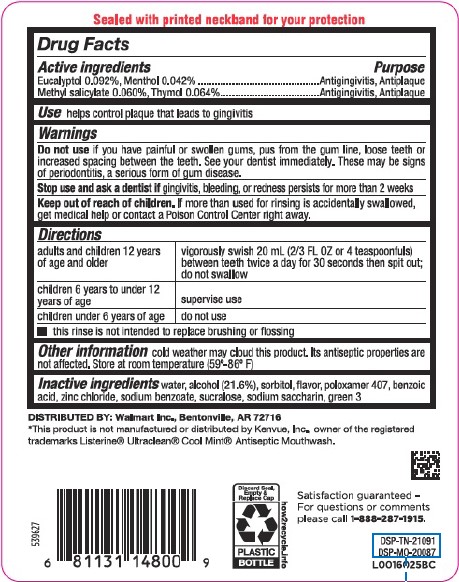 DRUG LABEL: Tartar control plus
NDC: 49035-855 | Form: MOUTHWASH
Manufacturer: Walmart Inc.
Category: otc | Type: HUMAN OTC DRUG LABEL
Date: 20260227

ACTIVE INGREDIENTS: EUCALYPTOL 0.92 mg/1 mL; MENTHOL 0.42 mg/1 mL; METHYL SALICYLATE 0.6 mg/1 mL; THYMOL 0.64 mg/1 mL
INACTIVE INGREDIENTS: WATER; ALCOHOL; SORBITOL; POLOXAMER 407; BENZOIC ACID; ZINC CHLORIDE; SODIUM BENZOATE; SUCRALOSE; SACCHARIN SODIUM; FD&C GREEN NO. 3

Equate 855.000/855AA-AC
Tartar Control Plus Antiseptic Mouth Rinse, Blue Mint

Tamper Evident Statement

Sealed with printed neckband for your protection

Active ingredients

Eucalyptol 0.092%

Menthol 0.042%

Methyl salicylate 0.060%

Thymol 0.064%

Purpose

Antigingivitis, antiplaque

Use

helps control plaque that leads to gingivitis

Warnings

For this product

Do not use

if you have painful or swollen gums, pus from the gum line, loose teeth or increased spacing between the teeth. See your dentist immediately. These may be signs of periodontitis, a serious form of gum disease.

Stop use and ask a dentist if

gingivitis, bleeding, or redness persists for more than 2 weeks.

Keep out of reach of children.

If more than used for rinsing is accidentally swallowed, get medical help or contact a Poison Control Center right away.

Directions

adults and children 12 years of age and older - vigorously swish 20 mL (2/3 FL OZ or 4 teaspoonfuls) between teeth twice a day for 30 seconds then spit out; do not swallow

children 6 years to under 12 years of age - supervise use

children under 6 years of age - do not use

- this rinse is not intended to replace brushing or flossing

Other information

cold weather may cloud this product. Its antiseptic properties are not affected. Store at room temperature (59°-86°F)

Inactive ingredients

water, alcohol (21.6%), sorbitol, flavor, poloxamer 407, benzoic acid, zinc chloride, sodium benzoate, sucralose, sodium saccharin, green 3

Disclaimer

*This product is not manufactured or distributed by Kenvue, Inc., owner of the registered trademarks Listerine® Ultraclean® Cool Mint® Antiseptic Mouthwash.

Adverse Reactions

DISTRIBUTED BY: Walmart Inc., Bentonville, AR 72716

Satisfaction guaranteed - For questions or comments please call 1-888-287-1915.

Discard Seal, Empty & Replace Cap

PLASTIC BOTTLE

how2recycle.info

DSP-TN-21091

DSP-MO-20087

principal display panel

NDC 49055-855-12

equate™

Compare to Listerine® Ultraclean® Cool Mint® Antiseptic Mouthwash active ingredients*

Tartar Control Plus Mputhwash

Antiseptic Mouth Rinse Plus

Antigingivitis/Antiplaque

Blue Mint

Long lasting clean feel

Controls tartar that can discolor teeth

Fresh breath with mouth-cooling sensation

Made in the USA with domestic and imported ingredients

Factory Certified

IMPORTANT: Read directions for proper use.

50.7 FL OZ (1.58 QT) 1.5 L